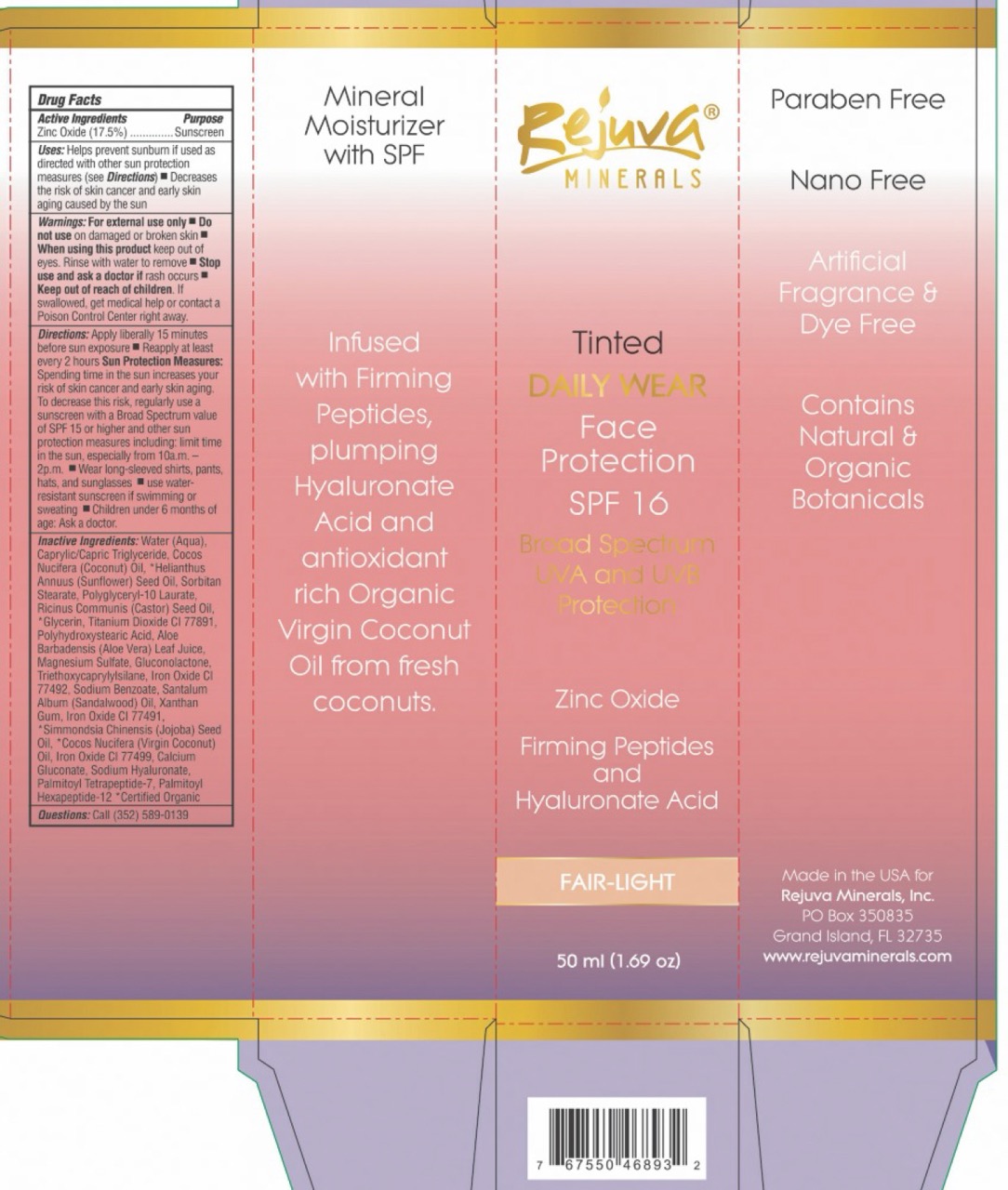 DRUG LABEL: Tinted Daily Wear Face Protection Mineral Based Sunscreen SPF 16 - Fair Light
NDC: 82328-0013 | Form: CREAM
Manufacturer: REJUVA MINERALS INC
Category: otc | Type: HUMAN OTC DRUG LABEL
Date: 20250102

ACTIVE INGREDIENTS: ZINC OXIDE 175 mg/1 mL
INACTIVE INGREDIENTS: RICINUS COMMUNIS (CASTOR) SEED OIL; TITANIUM DIOXIDE; POLYHYDROXYSTEARIC ACID (2300 MW); WATER; MEDIUM-CHAIN TRIGLYCERIDES; HELIANTHUS ANNUUS FLOWERING TOP; COCONUT OIL; SORBITAN MONOSTEARATE; POLYGLYCERYL-10 LAURATE; GLYCERIN; ALOE VERA LEAF; MAGNESIUM SULFATE, UNSPECIFIED FORM; GLUCONOLACTONE; TRIETHOXYCAPRYLYLSILANE; SODIUM BENZOATE; SANDALWOOD OIL; XANTHAN GUM; JOJOBA OIL; SUNFLOWER OIL; CALCIUM GLUCONATE; HYALURONATE SODIUM; PALMITOYL TETRAPEPTIDE-7; PALMITOYL HEXAPEPTIDE-12; IRON OXIDES

Rejuva Minerals Tinted Daily Wear Face Protection Mineral Based Sunscreen SPF 16 - Fair Light (50 ml / 1.69 oz)

Active Ingredients

Zinc Oxide (17.5%)

Purpose

Sunscreen

Uses:

Helps prevent sunburn if used as directed with other sun protection measures (see Directions)

- Decreases the risk of skin cancer and early skin aging caused by the sun

Warnings:

For external use only

Do not use

- on damaged or broken skin

When using this product

- keep out of eyes. Rinse with water to remove

Stop use and ask a doctor if

- rash occurs

Keep out of reach of children.

- If swallowed, get medical help or contact a Poison Control Center right away.

Directions:

Apply liberally 15 minutes before sun exposure

- Reapply at least every 2 hours Sun Protection Measures:Spending time in the sun increases your risk of skin cancer and early skin aging. To decrease this risk, regularly use a sunscreen with a Broad Spectrum value of SPF 15 or higher and other sun protection measures including: limit time in the sun, especially from 10a.m. – 2p.m.
- Wear long-sleeved shirts, pants, hats, and sunglasses
- use water resistant sunscreen if swimming or sweating
- Children under 6 months of age: Ask a doctor.

Inactive Ingredients:

Water (Aqua), Caprylic/Capric Triglyceride, Cocos Nucifera (Coconut) Oil, Helianthus Annuus (Sunflower) Oil, Sorbitan Stearate, Polyglyceryl-10 Laurate, Ricinus Communis (Castor) Seed Oil, Glycerin*, Titanium Dioxide CI 77891, Polyhydroxystearic Acid, Aloe Barbadensis Leaf Juice, Magnesium Sulfate, Gluconolactone, Triethoxycaprylylsilane, Iron Oxide CI 77492, Sodium Benzoate, Santalum Album (Sandalwood) Oil, Xanthan Gum, Iron Oxide CI 77491, Simmondsia Chinensis (Jojoba) Seed Oil*, Cocos Nucifera (Virgin Coconut) Oil*, Iron Oxide CI 77499, Calcium Gluconate, Sodium Hyaluronate, Palmitoyl Tetrapeptide-7, Palmitoyl Hexapeptide-12. *Certified Organic.

Questions:

Call (352) 589-0139

Package Labeling:

Rejuva
Minerals

Tinted
DAILY WEAR
Face
Protection
SPF 16
Broad Spectrum
UVA and UVB
Protection

Zinc Oxide

Firming Peptides
and
Hyaluronate Acid

FAIR-LIGHT

50 ml (1.69 oz)